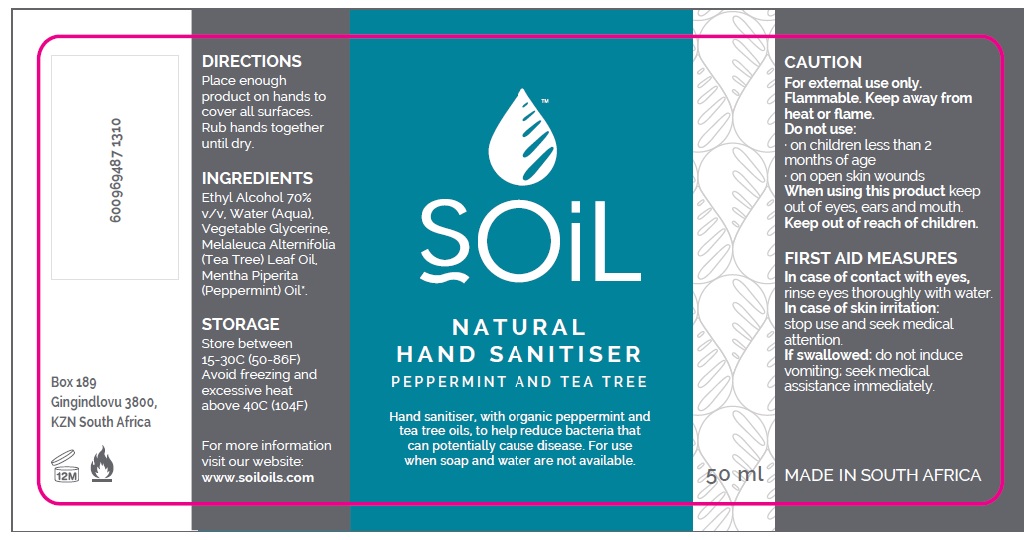 DRUG LABEL: SOiL Peppermint and Tea Tree Hand Sanitiser 50ml
NDC: 79213-003 | Form: LIQUID
Manufacturer: Veld Botanicals (Pty) Ltd
Category: otc | Type: HUMAN OTC DRUG LABEL
Date: 20200709

ACTIVE INGREDIENTS: ALCOHOL 70 mL/100 mL
INACTIVE INGREDIENTS: GLYCERIN 1.45 mL/100 mL; WATER; TEA TREE OIL 0.5 mL/100 mL; PEPPERMINT OIL 0.5 mL/100 mL

SOiL Peppermint and Tea Tree Sanitiser 50ml

Active Ingredient(s)

Alcohol 70% v/v. Purpose: Antiseptic

Purpose

Antiseptic, Hand Sanitizer

Use

Hand Sanitizer with organic peppermint and tea tree oils, to help reduce bacteria that potentially can cause disease. For use when soap and water are not available.

Warnings

For external use only. Flammable. Keep away from heat or flame

Do not use

- in children less than 2 months of age
- on open skin wounds

When using this product keep out of eyes, ears, and mouth.

Keep out of reach of children.

In case of contact with eyes, rinse eyes thoroughly with water.
In case of skin irritation stop use and seek medical attention.
If swallowed, do not induce vomiting, seek medical assistance immediately.

Stop use and ask a doctor if irritation or rash occurs. These may be signs of a serious condition.

Keep out of reach of children. If swallowed, get medical help or contact a Poison Control Center right away.

Directions

- Place enough product on hands to cover all surfaces. Rub hands together until dry.

Other information

- Store between 15-30C (59-86F)
- Avoid freezing and excessive heat above 40C (104F)

Inactive ingredients

glycerin, peppermint oil, tea tree oil, purified water USP

Package Label - Principal Display Panel

50 mL NDC: 79213-003-01